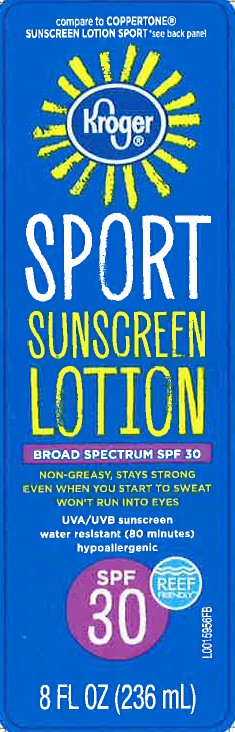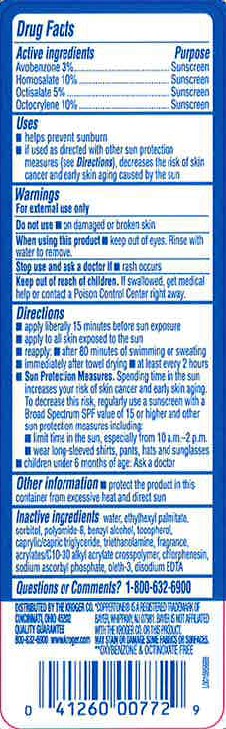 DRUG LABEL: Sunscreen
NDC: 30142-714 | Form: LOTION
Manufacturer: The Kroger Co.
Category: otc | Type: HUMAN OTC DRUG LABEL
Date: 20260227

ACTIVE INGREDIENTS: AVOBENZONE 30 mg/1 mL; HOMOSALATE 100 mg/1 mL; OCTISALATE 50 mg/1 mL; OCTOCRYLENE 100 mg/1 mL
INACTIVE INGREDIENTS: ETHYLHEXYL PALMITATE; SORBITOL; WATER; POLYAMIDE-8 (4500 MW); BENZYL ALCOHOL; TOCOPHEROL; MEDIUM-CHAIN TRIGLYCERIDES; TROLAMINE; CARBOMER INTERPOLYMER TYPE A (ALLYL SUCROSE CROSSLINKED); CHLORPHENESIN; SODIUM ASCORBYL PHOSPHATE; OLETH-3; EDETATE DISODIUM ANHYDROUS

Kroger 714.000/714AA
Sport Sunscreen Lotion SPF 30

Active Ingredients

Avobenzone 3%

Homosalate 10%

Octisalate 5%

Octocrylene 10%

Purpose

Sunscreen

Uses

- helps prevent sunburn
- if used as directed with other sun protections measures (see Directions), decreases the rist of skin cancer and early skin aging caused by the sun

Warnings

For external use only

Do not use

- on damaged or broken skin

When using this product

- keep out of eyes. Rinse with water to remove

Stop use and ask a doctor if

- rash occurs

Keep out of reach of children

If swallowed, get medical help or contact a Poison Control Center right away.

Directions

- apply liberally 15 minutes before sun exposure
- apply to all skin exposed to the sun
- reapply:
- after 80 minutes of swimming or sweating
- immediately after towel drying
- at least every 2 hours
- Sun Protection Measures. Spending time in the sun increases your risk of skin cancer and early skin aging. To decrease this risk, regularly use a sunscreen with a Broad Spectrum SPF value of 15 or higher and other sun protection measures including:
- limit time in the sun, especially from 10 a.m. - 2 p.m.
- wear long-sleeved shirts, pants, hats and sunglasses
- children under 6 months of age: Ask a doctor

Other Information

- Protect the product in this container from excessive heat and direct sun

Inactive ingredients

water, ethylhexyl palmitate, sorbitol, polyamide-8, benzyl alcohol, tocopherol, caprylic/capric triglyceride, triethanolamine, fragrance, acrylates/C10-30 alkyl acrylate crosspolymer, chlorphenesin, sodium ascorbyl phosphate, oleth-3, disodium EDTA

Questions or comments?

1-800-632-6900

Disclaimer

*COPPERTONE IS TRADEMARK OF BAYER, WHIPPANY, NJ 07981. BAYER IS NOT AFFILIATED WITH THE KROGER CO. OR THIS PRODUCT.

Adverse Reaction

DISTRIBUTED BY THE KROGER CO., CINCINNATI, OHIO 45202

QUALITY GUARANTEE

800-632-6900 www.kroger.com

May stain or damage some fabrics or surfaces.

Claims

**Oxybenzone & Octinoxate free

Principal display panel

compare to COPPERTONE®SUNSCREEN LOTION *see back panel

Kroger®

SPORT

SUNSCREEN

LOTION

BROAD SPECTRUM SPF 30

NON-GREASY, STAYS STRONG EVEN WHEN YOU START TO SWEAT

WON'T RUN INTO EYES

UVA/UVB sunscreen

water resistant (80 minutes)

hypoallergenic

SPF 30

REEF FRIENDLY**

8 FL OZ (236 mL)